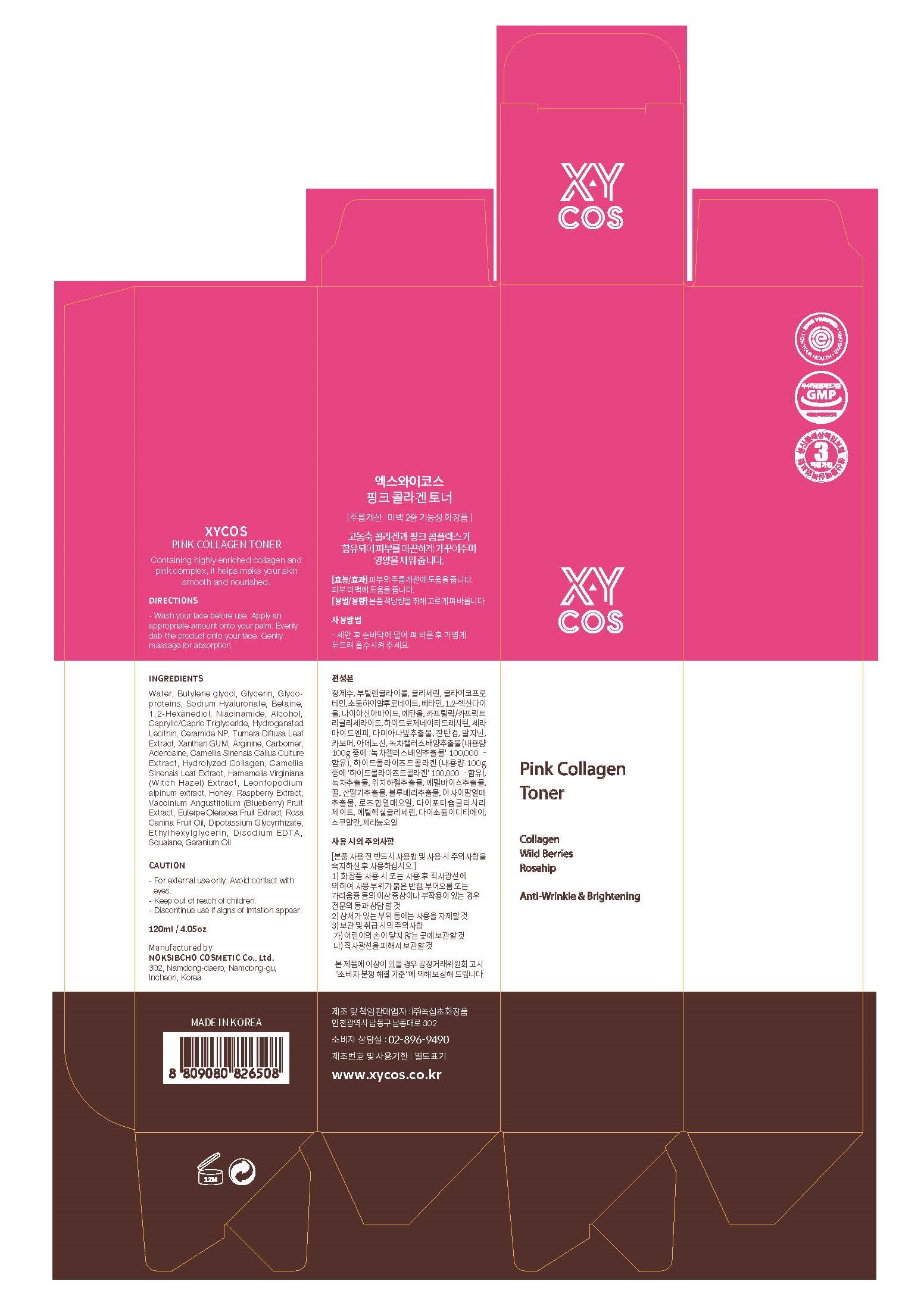 DRUG LABEL: XYCOS PINK COLLAGEN TONER
NDC: 73590-0047 | Form: LIQUID
Manufacturer: NOKSIBCHO cosmetic Co., Ltd.
Category: otc | Type: HUMAN OTC DRUG LABEL
Date: 20200331

ACTIVE INGREDIENTS: ADENOSINE 0.04 g/100 mL; NIACINAMIDE 2 g/100 mL
INACTIVE INGREDIENTS: WATER

Drug Facts

ACTIVE INGREDIENT

adenosine, niacinamide

INACTIVE INGREDIENT

Aqua
Butylene glycol
Glycerin
Betaine
1,2-Hexanediol
Niacinamide
Alcohol
Arginine
Polyacrylic acid
Caprylic/Capric Triglyceride
Rosa Canina Fruit Oil
Dipotassium Glycyrrhizate
GERANIUM OIL
Propylene Glycol
Ethylhexylglycerin
Adenosine
Sodium Hyaluronate
Phenoxy ethanol
Disodium EDTA
Hydrogenated Lecithin
Squalane
Camellia Sinensis Callus Culture Extract
Methyl Paraben
Turnera Diffusa Leaf Extract
ceramide NP
Leontopodium alpinum extract
Caprylyl Glycol
Camellia Sinensis Leaf Extract
Hamamelis Virginiana (Witch Hazel) Extract
Hydrolyzed Collagen
rasp berry Extract
Vaccinium Angustifolium (Blueberry) Fruit Extract
Euterpe Oleracea Fruit Extract
Tropolone

PURPOSE

anti-wrinkle & brightening

keep out of reach of the children

INDICATIONS AND USAGE

apply proper amount to the skin

WARNINGS

For external use only
When using this product

■ if the following symptoms occurs after use, stop use and consult with a skin specialist

red specks, swelling, itching

■ don’t use on the part where there is injury, eczema, or dermatitis

Keep out of reach of children

■ if swallowed, get medical help or contact a person control center immediately